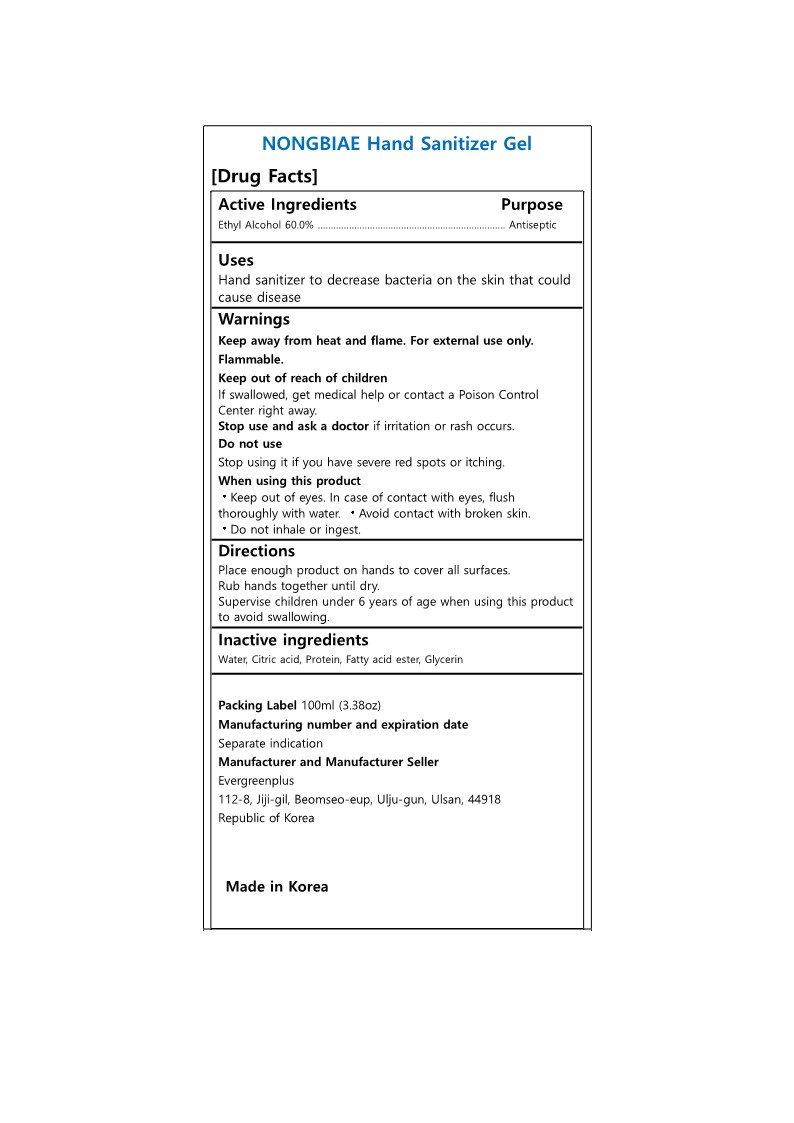 DRUG LABEL: NONGBIAE Hand Sanitizer
NDC: 82390-102 | Form: GEL
Manufacturer: Evergreenplus
Category: otc | Type: HUMAN OTC DRUG LABEL
Date: 20211116

ACTIVE INGREDIENTS: ALCOHOL 60 mL/100 mL
INACTIVE INGREDIENTS: WATER; CITRIC ACID MONOHYDRATE; GLYCERIN; HYDROLYZED ORYZANOL; ISOPROPYL BEHENATE

82390-102 NONGBIAE Hand Sanitizer

Active Ingredient

Ethyl Alcohol 60%

Purpose

Antiseptic

Uses

Hand sanitizer to decrease bacteria on the skin that could cause disease.

Warnings

Keep away from heat and flame. For external use only. Flammable.

Do not use

Stop using it if you have severe red spots or itching.

Keep out of reach of children

If swallowed, get medical help or contact a Poison Control Center right away.

Stop use

Stop use and ask a doctor if irritation or rash occurs.

When using

·Keep out of eyes. In case of contact with eyes, flush thoroughly with water. ·Avoid contact with broken skin.

·Do not inhale or ingest.

Directions

Place enough product on hands to cover all surfaces.

Rub hands together until dry.

Supervise children under 6 years of age when using this product to avoid swallowing.

Inactive Ingredients

Water, Citric acid, Protein, Fatty acid ester, Glycerin